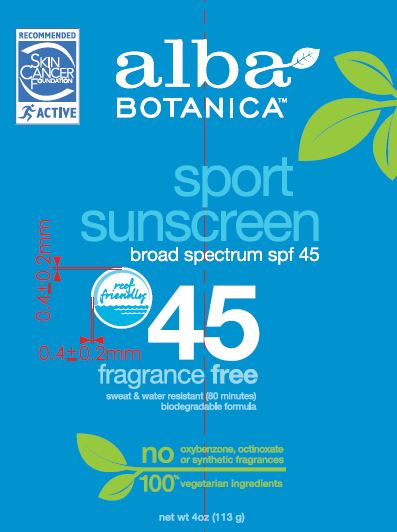 DRUG LABEL: Sport Sunscreen SPF 45
NDC: 61995-2020 | Form: LOTION
Manufacturer: The Hain Celestial Group, Inc
Category: otc | Type: HUMAN OTC DRUG LABEL
Date: 20221027

ACTIVE INGREDIENTS: AVOBENZONE 3 g/100 g; OCTOCRYLENE 10 g/100 g; OCTISALATE 5 g/100 g; HOMOSALATE 10 g/100 g
INACTIVE INGREDIENTS: MEDIUM-CHAIN TRIGLYCERIDES; ALCOHOL; XANTHAN GUM; CETEARYL OLIVATE; POLYSORBATE 60; SODIUM CHLORIDE; SODIUM STEAROYL GLUTAMATE; LAVANDULA ANGUSTIFOLIA FLOWER; CETOSTEARYL ALCOHOL; ANHYDROUS CITRIC ACID; SORBITAN OLIVATE; SODIUM BENZOATE; ALOE VERA WHOLE; BENZYL ALCOHOL; WATER; GLYCERYL STEARATE SE; POTASSIUM SORBATE; VINYLPYRROLIDONE/HEXADECENE COPOLYMER; CETYL ALCOHOL; GLYCERIN; GREEN TEA LEAF; MATRICARIA CHAMOMILLA FLOWERING TOP; GINKGO; ASIAN GINSENG; .ALPHA.-TOCOPHEROL ACETATE; CALENDULA OFFICINALIS FLOWER; DIMETHICONE

Alba Sport Sunscreen SPF 45

ACTIVE INGREDIENT

Avobenzone 3%

Homosalate 10%

Octocrylene 10%

Octisalate 5%

DOSAGE AND ADMINISTRATION

Apply liberally 15 minutes before sun exposure. Reapply after 80 minutes of swimming or sweating, immediately after towel drying and at least every 2 hours. Children under 6 months: ask a doctor. Sun Protection Measures: Spending time in the sun increases your risk of skin cancer and early skin aging. To decrease risk, regularly use a sunscreen with broad spectrum SPF 15 or higher and other protective measures including:

- limit time in the sun, especially from 10am to 2pm
- and wear long-sleeved shirts, pants, hats and sunglasses.

PURPOSE

Sunscreen

WARNINGS

For external use only. Do not use on broken or damaged skin. When using this product, keep out of eyes. Rinse with water to remove. Stop use and ask a doctor if skin rash occurs. If swallowed, get medical help or contact a Poison Control Center right away.

Keep out of reach of children.

INACTIVE INGREDIENT

Water (Aqua), Cetyl Alcohol, Glycerin, Glyceryl Stearate SE, Dimethicone, Caprylic/Capric Triglyceride, VP/Hexadecene Copolymer, Aloe Barbadensis Leaf Juice (1), Calendula Officinalis Flower Extract (1), Camellia Sinensis Leaf Extract (1), Chamomilla Recutita (Matricaria) Flower Extract (1), Ginkgo Biloba Leaf Extract, Lavandula Angustifolia (Lavender) Flower Extract (1), Panax Ginseng Root Extract, Tocopheryl Acetate, Alcohol (1), Cetearyl Alcohol, Cetearyl Olivate, Citric Acid, Polysorbate 60, Sodium Chloride, Sodium Stearoyl Glutamate, Sorbitan Olivate, Xanthan Gum, Benzyl Alcohol, Potassium Sorbate, Sodium Benzoate

(1) Certified Organic Ingredient

INDICATIONS AND USAGE

- Helps prevent sunburn
- If used as directed with other sun protection measures (see Directions), decreases the risk of skin cancer and early skin aging caused by the sun